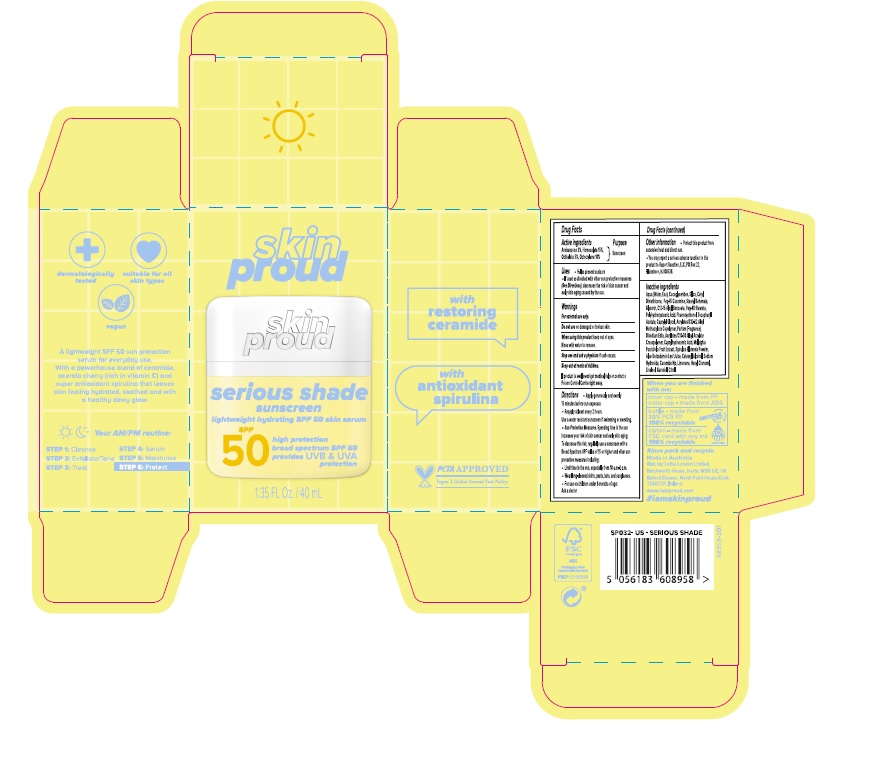 DRUG LABEL: Skin Proud Serious Shade Sunscreen SPF 50
NDC: 82803-001 | Form: EMULSION
Manufacturer: Lottie London Limited
Category: otc | Type: HUMAN OTC DRUG LABEL
Date: 20221026

ACTIVE INGREDIENTS: AVOBENZONE 30 mg/1 mL; HOMOSALATE 150 mg/1 mL; OCTISALATE 50 mg/1 mL; OCTOCRYLENE 100 mg/1 mL
INACTIVE INGREDIENTS: WATER; SILICON DIOXIDE; CETYL DIMETHICONE 25; PEG-15 COCAMINE; PEG-40 STEARATE; CAPRYLYL GLYCOL; ALOE VERA LEAF; CERAMIDE NP; SODIUM HYDROXIDE; GERANIOL; CITRAL; CARBOMER COPOLYMER TYPE B (ALLYL PENTAERYTHRITOL CROSSLINKED); LIMONENE, (+)-; .ALPHA.-HEXYLCINNAMALDEHYDE; LINALOOL, (+)-; STEARYL BEHENATE; ALKYL (C12-15) BENZOATE; CAPRYLHYDROXAMIC ACID; MALPIGHIA GLABRA FRUIT; GLYCERIN; POLYHYDROXYSTEARIC ACID (2300 MW); PHENOXYETHANOL; .ALPHA.-TOCOPHEROL ACETATE; CETOSTEARYL ALCOHOL; COCO-GLYCERIDES; EDETATE DISODIUM ANHYDROUS; SPIRULINA PLATENSIS

Skin Proud Serious Shade Sunscreen SPF 50

Active ingredients

Avobenzone 3%

Homosalate 15%

Octisalate 5%

Octocrylene 10%

Purpose

Sunscreen

Uses

- Helps prevent sunburn
- If used as directed with other sun protection measures (See Directions), decreases the risk of skin cancer and early skin aging caused by the sun.

Warnings

For external use only.

Do not use

on damaged or broken skin.

When using this product

keep out of eyes. Rinse with water to remove.

Stop use and ask a physician

if rash occurs.

Keep out of reach of children.

If product is swallowed get medical help or contact a Poison Control Centre right away.

Directions

- Apply generously and evenly 15 minutes before sun exposure.
- Reapply at least every 2 hours. Use a water resistant sunscreen if swimming or sweating.
- Sun Protection Measures: Spending time in the sun increases your risk of skin cancer and early skin aging. To decrease this risk, regularly use a sunscreen with a Broad Spectrum SPF value of 15 or higher and other sun protection measures including:
- Limit time in the sun, especially from 10 a.m.-2 p.m.
- Wear long-sleeved shirts, pants, hats, and sunglasses.
- For use on children under 6 months of age: Ask a doctor

Other information

- Protect this product from excessive heat and direct sun.
- You may report a serious adverse reaction to this product to Report Reaction, LLC, PO Box 22, Plainsboro, NJ 08536.

Inactive ingredients

Aqua (Water, Eau), Cocoglycerides, Silica, Cetyl Dimethicone, Peg-15 Cocamine, Stearyl Behenate, Glycerin, C12-15 Alkyl Benzoate, Peg-40 Stearate, Polyhydroxystearic Acid, Phenoxyethanol, Tocopheryl Acetate, Caprylyl Glycol, Acrylates/C12-22 Alkyl Methacrylate Copolymer, Parfum (Fragrance), Disodium Edta, Acrylates/C10-30 Alkyl Acrylate Crosspolymer, Caprylhydroxamic Acid, Malpighia Punicifolia Fruit Extract, Spirulina Platensis Powder, Aloe Barbadensis Leaf Juice, Cetearyl Alcohol, Sodium Hydroxide, Ceramide Np, Limonene, Hexyl Cinnamal, Linalool, Geraniol, Citral.

Company Information

Made in Australia

Dist. by: Lottie London Limited, Batchworth House, Herts, WD3 1JE, UK Oxford Eireann, North Point House, Cork, T23AT2P, Ireland

www.iamproud.com